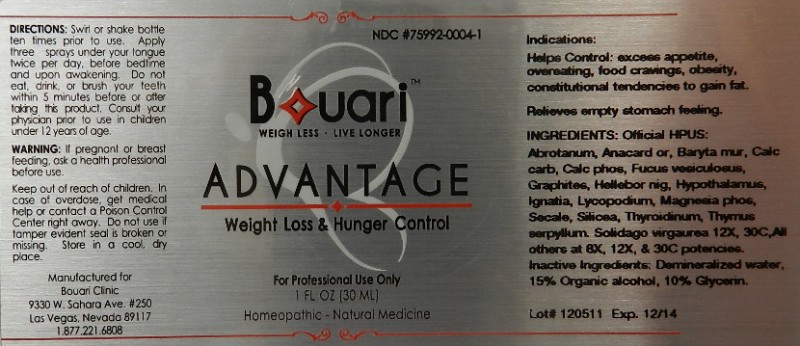 DRUG LABEL: Advantage Weight Loss and Hunger Control
NDC: 75992-0004 | Form: LIQUID
Manufacturer: Bouari Clinic
Category: homeopathic | Type: HUMAN OTC DRUG LABEL
Date: 20111207

ACTIVE INGREDIENTS: ARTEMISIA ABROTANUM FLOWERING TOP 8 [hp_X]/30 mL; SEMECARPUS ANACARDIUM JUICE 8 [hp_X]/30 mL; BARIUM CHLORIDE DIHYDRATE 8 [hp_X]/30 mL; OYSTER SHELL CALCIUM CARBONATE, CRUDE 8 [hp_X]/30 mL; TRIBASIC CALCIUM PHOSPHATE 8 [hp_X]/30 mL; FUCUS VESICULOSUS 8 [hp_X]/30 mL; GRAPHITE 8 [hp_X]/30 mL; HELLEBORUS NIGER ROOT 8 [hp_X]/30 mL; BOS TAURUS HYPOTHALAMUS 8 [hp_X]/30 mL; STRYCHNOS IGNATII SEED 8 [hp_X]/30 mL; LYCOPODIUM CLAVATUM SPORE 8 [hp_X]/30 mL; MAGNESIUM PHOSPHATE, DIBASIC TRIHYDRATE 8 [hp_X]/30 mL; CLAVICEPS PURPUREA SCLEROTIUM 8 [hp_X]/30 mL; SILICON DIOXIDE 8 [hp_X]/30 mL; SOLIDAGO VIRGAUREA FLOWERING TOP 12 [hp_X]/30 mL; THYROID, UNSPECIFIED 8 [hp_X]/30 mL; THYMUS SERPYLLUM 8 [hp_X]/30 mL
INACTIVE INGREDIENTS: WATER; ALCOHOL; GLYCERIN

Advantage Weight Loss and Hunger Control

Active Ingredient

Official HPUS: Abrotanum, Anacardium Orientale, Baryta Muriatica, Calcarea Carbonica, Calcarea Phosphorica, Fucus Vesiculosus, Graphites, Helleborus Niger, Hypothalamus, Ignatia Amara, Lycopodium Clavatum, Magnesia Phosphorica, Secale Cornutum, Silicea, Thyroidinum, and Thymus Serpyllum at 8X, 12X and 30C. Solidago Virgaurea 12X and 30C.
Reference image weight loss.jpg

Inactive Ingredients

Demineralized water

15% Organic alcohol

10% Glycerin

Reference image weight loss.jpg

Dosage And Administration

Directions: Swirl or shake bottle ten times prior to use. Apply three sprays under your tongue twice per day, before bedtime and upon awakening. Do not eat, drink, or brush your teeth within 5 minutes before or after taking this product. Consult your physician prior to use in children under 12 years of age.

Reference image weight loss.jpg

Warnings

If pregnant or breast feeding, ask a health professional before use. Keep out of reach of children. In case of overdose, get medical help or contact a Poison Control Center right away.

Do not use if tamper evident seal is broken or missing. Store in a cool, dry place.

Reference weight loss.jpg

Keep out of reach of children.

Reference image weight loss.jpg

Purpose

Helps Control:

- excess appetite
- overeating
- food cravings
- obesity, constitutional tendencies to gain fat
- relieves empty stomach feeling

Reference image weight loss.jpg

Indications

Helps Control: excess appetite, overeating, food cravings, obesity, constitutional tendencies to gain fat.

Relieves empty stomach feeling.

Reference image weight loss.jpg

PACKAGE LABEL

Bouari Clinic

9330 W. Sahara Ave. #250

Las Vegas, Nevada 89117

1 877.221.6808